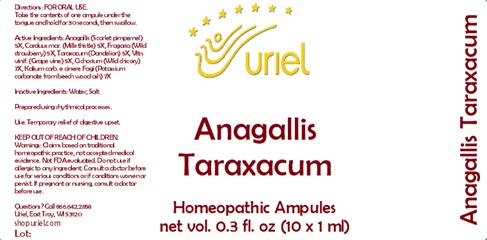 DRUG LABEL: Anagallis Taraxacum
NDC: 48951-1030 | Form: LIQUID
Manufacturer: Uriel Pharmacy Inc.
Category: homeopathic | Type: HUMAN OTC DRUG LABEL
Date: 20241218

ACTIVE INGREDIENTS: ANAGALLIS ARVENSIS 5 [hp_X]/1 mL; MILK THISTLE 5 [hp_X]/1 mL; FRAGARIA VESCA WHOLE 5 [hp_X]/1 mL; TARAXACUM PALUSTRE ROOT 5 [hp_X]/1 mL; VITIS VINIFERA LEAF 5 [hp_X]/1 mL; CICHORIUM INTYBUS WHOLE 7 [hp_X]/1 mL; POTASSIUM CARBONATE 7 [hp_X]/1 mL
INACTIVE INGREDIENTS: WATER; SODIUM CHLORIDE

Anagallis Taraxacum

INDICATIONS AND USAGE

Directions: FOR ORAL USE.

DOSAGE AND ADMINISTRATION

Take the contents of one ampule under the tongue and hold for 30 seconds, then swallow.

ACTIVE INGREDIENT

Active Ingredients: Anagallis (Scarlet pimpernel) 5X, Carduus mar. (Milk thistle) 5X, Fragaria (Wild strawberry) 5X, Taraxacum (Dandelion) 5X, Vitis vinif. (Grape vine) 5X, Cichorium (Wild chicory) 7X, Kalium carb. e cinere Fagi (Potassium carbonate from beech wood ash) 7X

Inactive Ingredients: Water, Salt

Prepared using rhythmical processes.

PURPOSE

Use: Temporary relief of digestive upset.

KEEP OUT OF REACH OF CHILDREN.

WARNINGS

Warnings: Claims based on traditional homeopathic practice, not accepted medical evidence. Not FDA evaluated. Do not use if allergic to any ingredient. Consult a doctor before use for serious conditions or if conditions worsen or persist. If pregnant or nursing, consult a doctor before use.

QUESTIONS

Questions? Call 866.642.2858 Uriel, East Troy, WI 53120 shopuriel.com Lot: